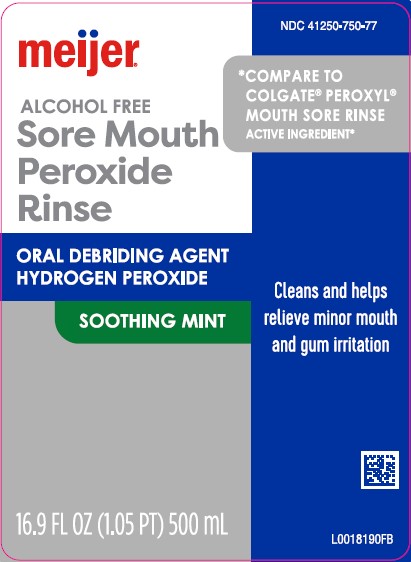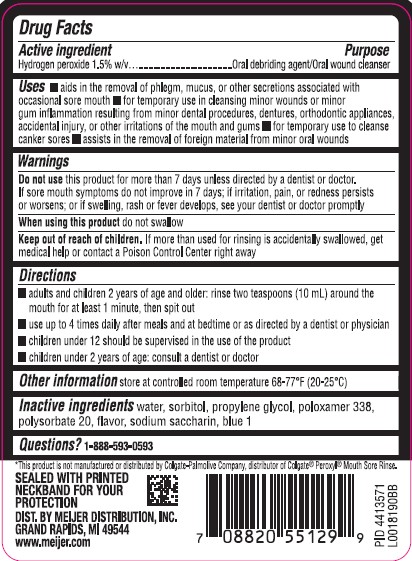 DRUG LABEL: Sore Mouth Cleanser
NDC: 41250-750 | Form: MOUTHWASH
Manufacturer: Meijer, Inc.
Category: otc | Type: HUMAN OTC DRUG LABEL
Date: 20260219

ACTIVE INGREDIENTS: HYDROGEN PEROXIDE 15 mg/1 mL
INACTIVE INGREDIENTS: WATER; SORBITOL; PROPYLENE GLYCOL; POLOXAMER 338; POLYSORBATE 20; SACCHARIN SODIUM; FD&C BLUE NO. 1

Meijer 462.002 /462AA rev 1
Alcohol-Free Mint Peroxide Rinse

Active ingredient

Hydrogen peroxide 1.5% w/v

Purpose

Oral debriding agent/Oral wound cleanser

Uses

- aids in the removal of phlgem, mucus, or other secretions associated with occasional sore mouth
- for temporary use in cleansing minor wounds or minor gum inflammation resulting from minor dental procedures, dentures, orthodontic appliances, acidental injury, or other irritations of the mouth and gums
- for temporary use to cleanse canker sores
- assists in the removal of foreign material from minor oral wounds

Warnings

For this product

Do not use

this product for more than 7 days unless directed by a dentist or doctor. If sore mouth symptoms do not improve in 7 days; if irritation, pain, or redenss persists or worsens; or if swelling, rash or fever develops, see your dentist or doctor promptly

When using this product

do not swallow

Keep out of reach of children.

If more than used for rinsing is accidentally swallowed, get medical help or contact a Poison Control Center right away.

Directions

- adults and children 2 years of age and older: rinse two teaspoons (10 mL) around the mouth for at least 1 minute, then spit out
- use up to 4 times daily after meals and at bedtime or as directed by a dentist or physician
- children under 12 should be supervised in the use of the product
- children under 2 years of age: consult a dentist or doctor

Other information

store at controlled room temperature 68-77°F (20-25°C)

Inactive ingredients

water, sorbitol, propylene glycol, poloxamer 338, polysorbate 20, flavor, sodium saccharin, blue 1

Questions?

1-888-593-0593

Disclaimer

*This product is not manufactured or distributed by Colgate-Palmolive Company, distributor of Colgate® Peroxyl® Mouth Sore Rinse.

Tamper Evident Statement

SEALED WITH PRINTED NECKBAND FOR YOUR PROTECTION

Adverse Reactions

DIST. BY MEIJER DISTRIBUTION, INC.

GRAND RAPIDS, MI 49544

www.meijer.com

PID 4413571

Principal display panel

NDC 41250-750-77

meijer®

*COMPARE TO COLGATE®PEROXYL® MOUTH SORE RINSE ACTIVE INGREDIENT*

ALCOHOL FREE

Sore Mouth Peroxide Rinse

ORAL DEBRIDING AGENT

HYGROGEN PEROXIDE

SOOTHING MINT

Cleans and helps relieve minor mouth and gum irritation

16.9 FL OZ (1.05 PT) 500 mL